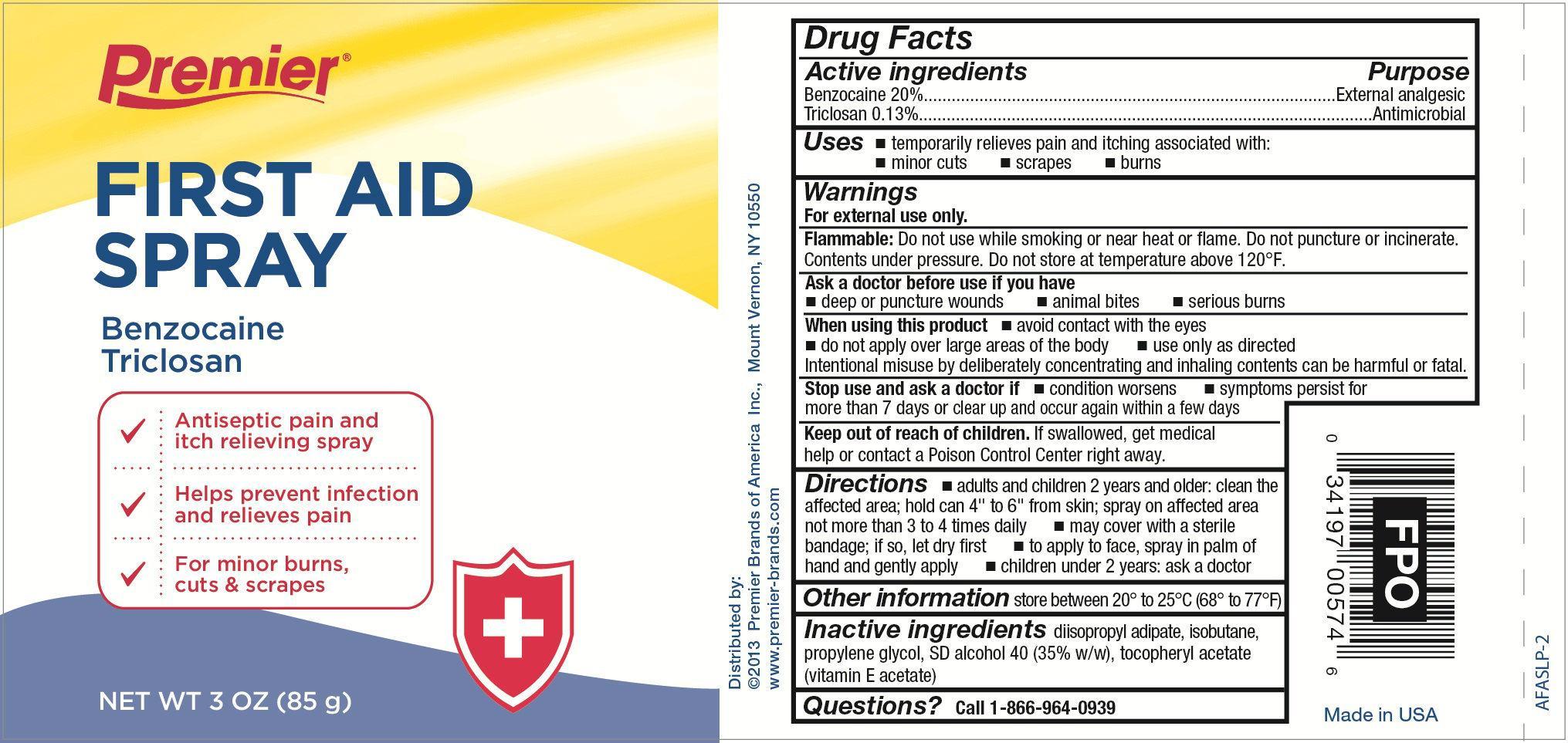 DRUG LABEL: Benzocaine and Triclosan
NDC: 56104-005 | Form: AEROSOL, SPRAY
Manufacturer: Premier Brands of America Inc.
Category: otc | Type: HUMAN OTC DRUG LABEL
Date: 20151231

ACTIVE INGREDIENTS: BENZOCAINE 17 g/85 g; TRICLOSAN 0.11 g/85 g
INACTIVE INGREDIENTS: DIISOPROPYL ADIPATE; ISOBUTANE; PROPYLENE GLYCOL; ALCOHOL; .ALPHA.-TOCOPHEROL ACETATE

First Aid Spray

Active ingredient

Benzocaine 20%
Triclosan 0.13%

Purpose

External analgesic
Antimicrobial

Uses

temporary relieves pain and itching associated with:

- minor cuts
- scrapes
- burns

Warnings

For external use only.

Flammable:

Do not use while smoking or near heat or flame. Do not puncture or incinerate. Contents under pressure. Do not store at temperature above 120ºF

Ask a doctor before use if you

- deep or puncture wounds
- animal bites
- serious burns

When using this product

- avoid contact with the eyes
- do not apply over large area of the body
- use only as directed

Intentional misuse by deliberately concentrating and inhaling the contents can be harmful or fatal.

Stop use and ask a doctor if

- conditions worsens
- symptoms persists for more than 7 days or clear up and occur again within a few days

Keep out of reach of children.

If swallowed, get medical help or contact a Poison Control Center right away.

Directions

- adults and children 2 years and older: clean the affected area; hold can 4" to 6" from skin; spray on affected area not more than 3 to 4 times daily
- may cover with a sterile bandage; if so, let dry first
- to apply to face, spray in palm of hand and gently apply
- children under 2 years: ask a doctor

Other information

store between 20º and 25ºC (68ºF and 77º)

Inactive ingredients

diisopropyl adipate, isobutane, propylene glycol, SD alcohol 40 (35%w/w), tocopheryl acetate (vitamin E acetate)

Questions?

call 1-866-964-0939

Principal Display Panel

Premier

First Aid Spray
Maximum Strength

Benzocaine 20% / Triclosan 0.13%

- External analgesic pain & itch relief spray
- For minor burns, cuts, scrapes & insect bites

Net WT 3 OZ (127 g)